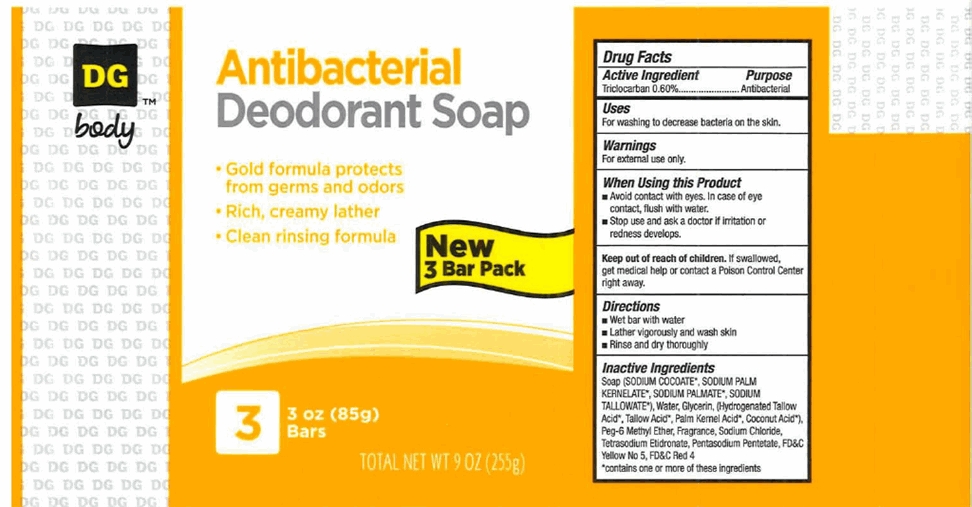 DRUG LABEL: Dollar General Gold
NDC: 55910-301 | Form: SOAP
Manufacturer: Dolgencorp, LLC
Category: otc | Type: HUMAN OTC DRUG LABEL
Date: 20120329

ACTIVE INGREDIENTS: TRICLOCARBAN .60 g/100 g
INACTIVE INGREDIENTS: SODIUM COCOATE; SODIUM PALM KERNELATE; SODIUM TALLOWATE, BEEF; WATER; GLYCERIN; TALLOW ACID, BEEF; COCONUT ACID; PEG-6 METHYL ETHER; SODIUM CHLORIDE; ETIDRONATE TETRASODIUM; PENTASODIUM PENTETATE; FD&C YELLOW NO. 5; FD&C RED NO. 4

Drug Facts - DG™ body Antibacterial Deodorant Soap

Active ingredient

Triclocarban 0.60%

Purpose

Antibacterial

Uses

For washing to decrease bacteria on the skin.

Warnings

For external use only.

When Using this Product

- Avoid contact with eyes. In case of eye contact, flush with water.
- Stop use and ask a doctor if irritation or redness develops.

Keep Out of Reach of Children.

If swallowed, get medical help or contact a Poison Control Center right away.

Directions

- Wet bar with water
- Lather vigorously and wash skin
- Rinse and dry thoroughly

Inactive ingredients

Soap (SODIUM COCOATE*, SODIUM PALM KERNELATE*, SODIUM PALMATE*, SODIUM TALLOWATE*), Water, Glycerin, (Hydrogenated Tallow Acid*, Tallow Acid*, Palm Kernel Acid*, Coconut Acid*), Pet-6 Methyl Ether, Fragrance, Sodium Chloride, Tetrasodium Etidronaet, Pentasodium Pentetate, FD&C Yellow No 5, FD&C Red 4

*contains one or more of these ingredients

Package/Label Principal Display Panel - 3 Bar Pack Label

3 Bar Pack Label

DG™

body

Antibacterial

Deodorant Soap

- Gold formula protects from germs and odors
- Rich, creamy lather
- Clean rinsing formula

New

3 Bar Pack

3 3 oz (85g) Bars

TOTAL NET WT 9 OZ (255g)